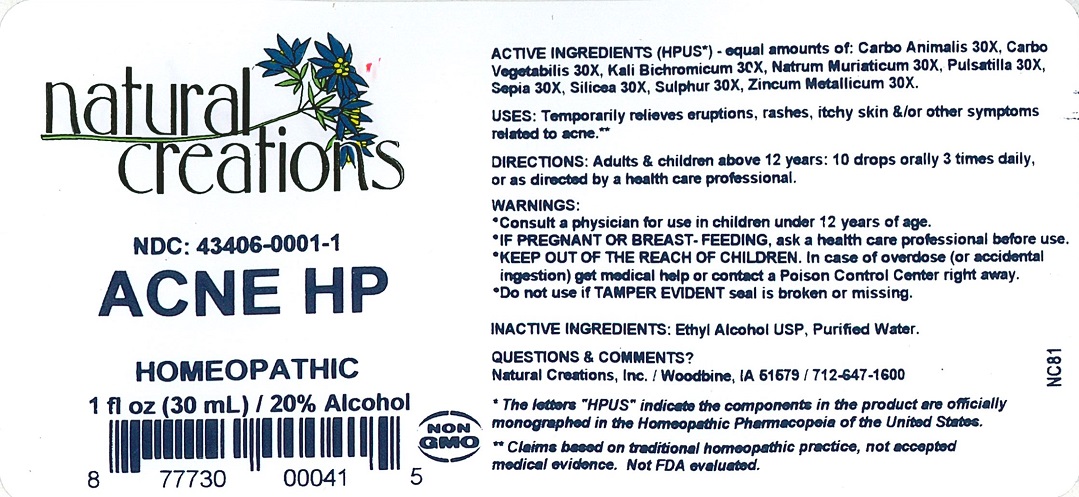 DRUG LABEL: ACNE HP
NDC: 43406-0001 | Form: LIQUID
Manufacturer: Natural Creations, Inc.
Category: homeopathic | Type: HUMAN OTC DRUG LABEL
Date: 20220214

ACTIVE INGREDIENTS: CARBO ANIMALIS 30 [hp_X]/1 mL; ACTIVATED CHARCOAL 30 [hp_X]/1 mL; POTASSIUM DICHROMATE 30 [hp_X]/1 mL; SODIUM CHLORIDE 30 [hp_X]/1 mL; PULSATILLA VULGARIS WHOLE 30 [hp_X]/1 mL; SEPIA OFFICINALIS JUICE 30 [hp_X]/1 mL; SILICON DIOXIDE 30 [hp_X]/1 mL; SULFUR 30 [hp_X]/1 mL; ZINC 30 [hp_X]/1 mL
INACTIVE INGREDIENTS: WATER; ALCOHOL

ACNE HP

ACTIVE INGREDIENT

ACTIVE INGREDIENTS (HPUS*) - equal amounts of: Carbo Animalis 30X, Carbo Vegetabilis 30X, Kali Bichromicum 30X, Natrum Muriaticum 30X, Pulsatilla 30X, Sepia 30X, Silicea 30X, Sulphur 30X, Zincum Metallicum 30X.

PURPOSE

USES: Temporarily relieves eruptions, rashes, itchy skin &/or other symptoms related to acne.**

INDICATIONS AND USAGE

USES: Temporarily relieves eruptions, rashes, itchy skin &/or other symptoms related to acne.**

DOSAGE AND ADMINISTRATION

DIRECTIONS: Adults & children above 12 years, 10 drops orally 3 times daily, or as directed by a health care professional.

KEEP OUT OF REACH OF CHILDREN

KEEP OUT OF THE REACH OF CHILDREN. In case of overdose (or accidental ingestion) get medical help or contact a Poison Control Center right away.

WARNINGS:

- Consult a physician for use in children under 12 years of age.
- IF PREGNANT OR BREAST-FEEDING, ask a health care professional before use.
- KEEP OUT OF THE REACH OF CHILDREN. In case of overdose (or accidental ingestion) get medical help or contact a Poison Control Center right away.
- Do not use if TAMPER EVIDENT seal is broken or missing.

INACTIVE INGREDIENT

INACATIVE INGREDIENTS: Ethyl Alcohol USP, Purified Water.

Questions & Comments?

Natural Creations, Inc. / Woodbine, IA 51579 / 712-647-1600

REFERENCES

*The letters "HPUS" indicate the components in the product are officially monographed in the Homeopathic Pharmacopeia of the United States.

**Claims based on traditional homeopathic practice, not accepted medical evidence. Not FDA evaluated.

PACKAGE LABEL

43406-0001-1

ACNE HP

HOMEOPATHIC

1 fl oz (30 mL) / 20% Alcohol

UPC: 877730000415